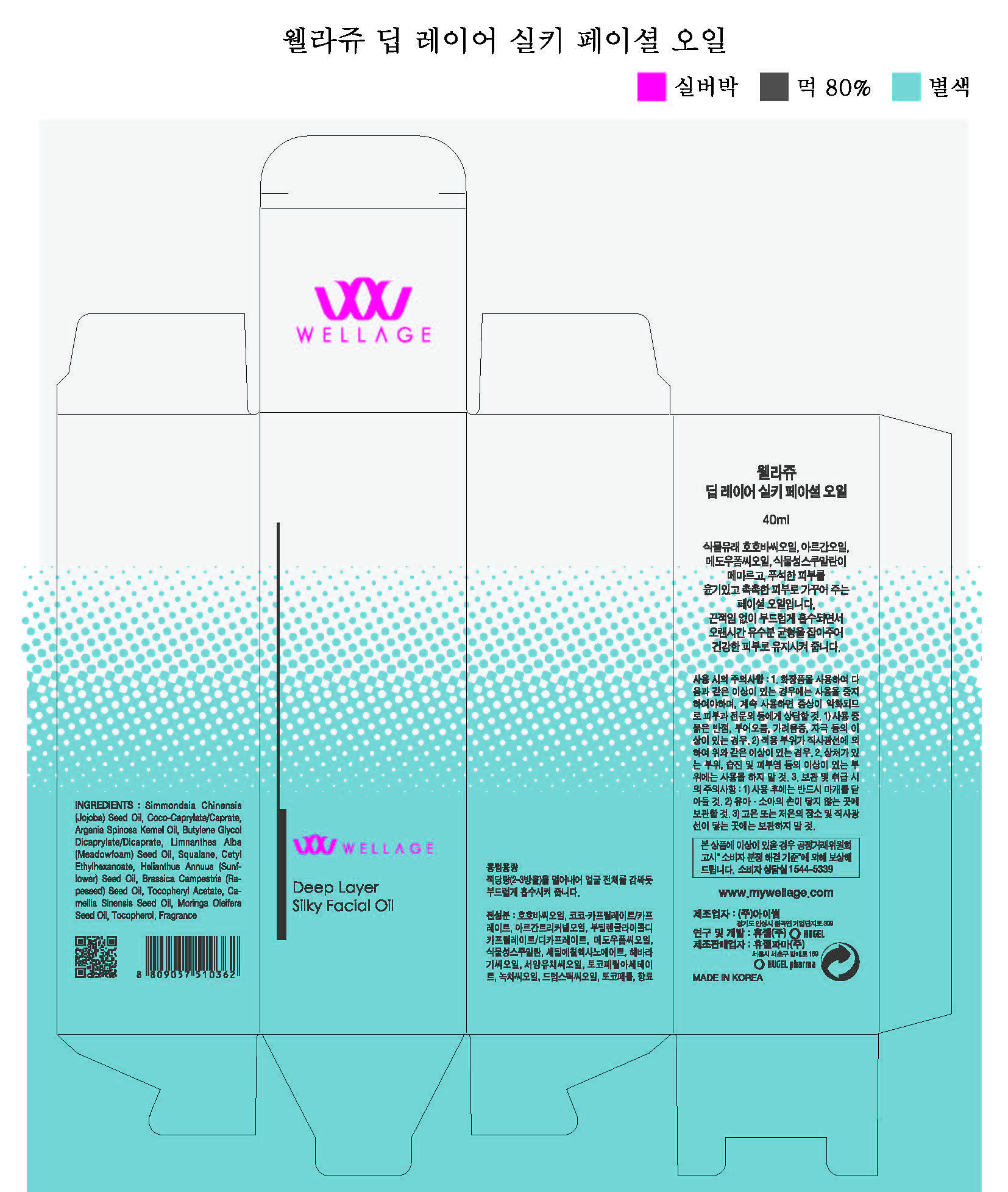 DRUG LABEL: WELLAGE Deep Layer Silky Facial Oil
NDC: 69346-0005 | Form: OIL
Manufacturer: HUGEL PHARMA CO.,LTD
Category: otc | Type: HUMAN OTC DRUG LABEL
Date: 20160908

ACTIVE INGREDIENTS: MEADOWFOAM SEED OIL 6 g/100 mL; SQUALANE 6 g/100 mL; ARGAN OIL 15 g/100 mL; SIMMONDSIA CHINENSIS SEED 35.1995 g/100 mL
INACTIVE INGREDIENTS: BUTYLENE GLYCOL DICAPRYLATE/DICAPRATE

Drug Facts

ACTIVE INGREDIENT

Simmondsia Chinensis (Jojoba) Seed Oil, Argania Spinosa Kernel Oil, Limnanthes Alba (Meadowfoam) Seed Oil, Squalane

INACTIVE INGREDIENT

Butylene Glycol Dicaprylate/Dicaprate

PURPOSE

Skin Protectant

keep out of reach of the children

INDICATIONS AND USAGE

Apply proper amount to the skin

WARNINGS

・Stop using the product when you have skin problems or the product disagrees with your skin
・Stop using the product immediately and consult a dermatologist if you have redness, swelling, itching or irritation on the skin while or after using the product.
・If the product gets into the eyes, don't rub but rinse with water.
・Don't place the product in any place where it will be subjected to extremely high or low temperatures or direct sunlight.

DOSAGE AND ADMINISTRATION

for external use only